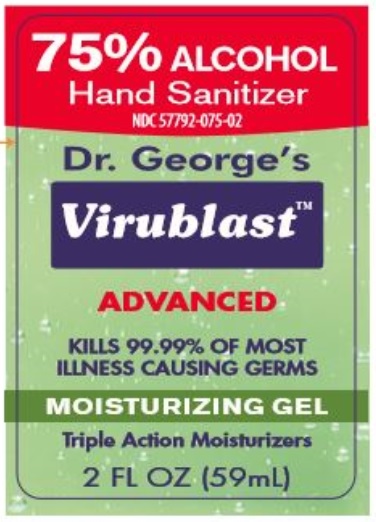 DRUG LABEL: Dr Georges Virublast
NDC: 57792-075 | Form: GEL
Manufacturer: M&M Innovations Inc
Category: otc | Type: HUMAN OTC DRUG LABEL
Date: 20200803

ACTIVE INGREDIENTS: ALCOHOL 75 mL/100 mL
INACTIVE INGREDIENTS: CARBOMER INTERPOLYMER TYPE A (55000 CPS); CAPRYLYL GLYCOL; WATER; AMINOMETHYLPROPANOL; .ALPHA.-TOCOPHEROL ACETATE; ALOE VERA LEAF; GLYCERIN; ISOPROPYL MYRISTATE; ISOPROPYL ALCOHOL

Dr Georges Virublast

Active ingredient

Ethyl Alcohol 75% v/v

Purpose

Handwash, antiseptic

Use

For handwashing to decrease bacteria on the skin.

Warnings

Flammable. Keep away from fire or flame.

For external use only.

Do not use in or near the eyes, in case of contact rinse eyes thoroughly with water

Stop use and ask a doctor if irritation or redness develop and persists for more than 72 hours.

Keep out of reach of children. If swallowed, get medical help or contact a Poison Control Center right away.

Directions

- wet hands thoroughly with product
- briskly rub hands together until dry
- supervise children in the use of this product

Other information

- store below 110F or 43C
- may discolor certain fabrics or surfaces

Inactive ingredients

water, isopropyl alcohol, aloe barbadensis leaf juice, caprylyl glycol, glyercin, isopropyl myristate, tocopheryl acetate, acrylates/c-10-30 alkyl acrylate crosspolymer, aminomethyl propanol, fragrance

Principal display panel

2 fl oz (59 ml)